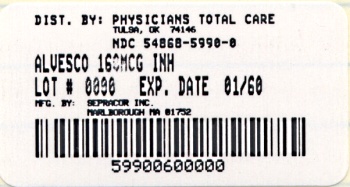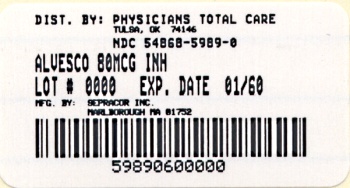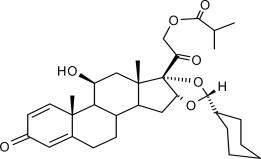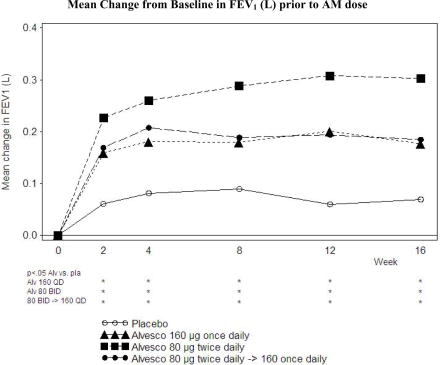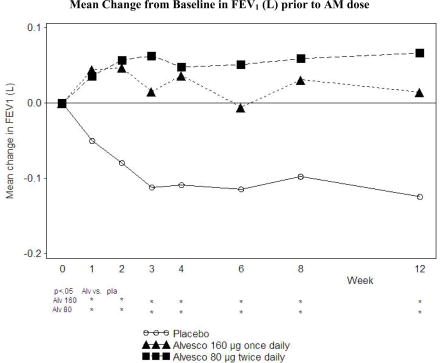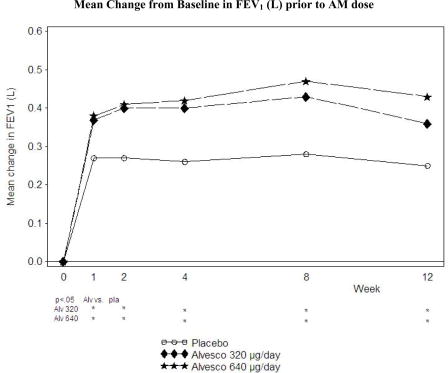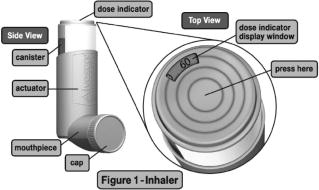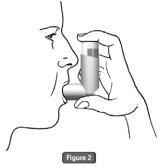 DRUG LABEL: Alvesco
NDC: 54868-5989 | Form: AEROSOL, METERED
Manufacturer: Physicians Total Care, Inc.
Category: prescription | Type: HUMAN PRESCRIPTION DRUG LABEL
Date: 20080701

ACTIVE INGREDIENTS: CICLESONIDE 80 ug/1 1
INACTIVE INGREDIENTS: NORFLURANE; ALCOHOL

HIGHLIGHTS OF PRESCRIBING INFORMATION

These highlights do not include all the information needed to use ALVESCO® safely and effectively. See full prescribing information for ALVESCO®.
ALVESCO® (ciclesonide) Inhalation Aerosol 80 mcg, 160 mcg
For Oral Inhalation Only
Initial U.S. Approval: 2006

1 INDICATIONS AND USAGE

ALVESCO is an inhaled corticosteroid indicated for: Maintenance treatment of asthma as prophylactic therapy in adult and adolescent patients 12 years of age and older. (1)

ALVESCO is NOT indicated for the relief of acute bronchospasm. (1)

2 DOSAGE AND ADMINISTRATION

FOR ORAL INHALATION ONLY (2.1)

 | Recommended; Starting Dose | Highest; Recommended Dose
Patients ≥ 12 years who received bronchodilators alone | 80 mcg twice daily | 160 mcg twice daily
Patients ≥ 12 years who received inhaled corticosteroids | 80 mcg twice daily | 320 mcg twice daily
Patients ≥ 12 years who received oral corticosteroids^1 | 320 mcg twice daily | 320 mcg twice daily
^1Prednisone should be reduced gradually, no faster than 2.5 mg/day on a weekly basis, beginning after at least 1 week of therapy with ALVESCO. Patients should be carefully monitored for signs of asthma instability, including monitoring of serial objective measures of airflow, and for signs of adrenal insufficiency during steroid taper and following discontinuation of oral corticosteroid therapy [see Warnings and Precautions (5.1)].

3 DOSAGE FORMS AND STRENGTHS

Inhalation Aerosol 80 mcg /actuation or 160 mcg /actuation (3)

4 CONTRAINDICATIONS

- Patients with status asthmaticus or other acute episodes of asthma where intensive measures are required (4.1)
- Patients with a known hypersensitivity to ciclesonide or any of the ingredients of ALVESCO.

5 WARNINGS AND PRECAUTIONS

- Candida albicans infection of the mouth and pharynx. Monitor patients periodically for signs of adverse effects on the oral cavity. Advise patients to rinse mouth following inhalation (5.1)
- Potential worsening of existing tuberculosis: fungal, bacterial, viral, or parasitic infection; or ocular herpes simplex. More serious or even fatal course of chickenpox or measles in susceptible patients. Use caution in patients with above because of the potential for worsening of these infections (5.3)
- Risk of impaired adrenal function when transferring from oral steroids to inhaled corticosteroids. Taper patients slowly from systemic corticosteroids if transferring to ALVESCO (5.4)
- Hypercorticism, suppression of hypothalamic-pituitary-adrenal (HPA) function with very high dosages or at the regular dosage in susceptible individuals. If such changes occur discontinue ALVESCO slowly (5.5)
- Suppression of growth in children. Monitor growth routinely in pediatric patients receiving ALVESCO (5.7)
- Development of glaucoma, increased intraocular pressure and posterior subcapsular cataracts. Monitor patients with a change in vision or with a history of increased intraocular pressure, glaucoma, and/or cataracts closely (5.8)

6 ADVERSE REACTIONS

Most common adverse reactions (≥3%) are headache, nasopharyngitis, sinusitis, pharyngolaryngeal pain, upper respiratory infection, arthralgia, nasal congestion, pain in extremity and back pain (6)

Other adverse reactions have been reported (6)

To report SUSPECTED ADVERSE REACTIONS, contact Sepracor Inc. at 1-877-737-7226 or FDA at 1-800-FDA-1088 or www.fda.gov/medwatch.

For customer service, call 1-888-394-7377
For medical information, call 1-800-739-0565

FULL PRESCRIBING INFORMATION

1 INDICATIONS AND USAGE

1.1 Treatment of Asthma

ALVESCO is indicated for the maintenance treatment of asthma as prophylactic therapy in adult and adolescent patients 12 years of age and older.

Important Limitations of Use:
ALVESCO is NOT indicated for the relief of acute bronchospasm.
ALVESCO is NOT indicated for children under 12 years of age.

2 DOSAGE AND ADMINISTRATION

ALVESCO should be administered by the orally inhaled route. Prime ALVESCO Inhalation Aerosol before using for the first time by actuating 3 times prior to using the first dose from a new canister or when the inhaler has not been used for more than 10 days. Individual patients will experience a variable time to onset and degree of symptom relief. Maximum benefit may not be achieved for four weeks or longer after initiation. After asthma stability has been achieved, it is desirable to titrate to the lowest effective dosage to reduce the possibility of side effects. For patients who do not respond adequately to the starting dose after 4 weeks of therapy, higher doses may provide additional asthma control. The safety and efficacy of ALVESCO when administered in excess of the highest recommended doses has not been established.

Recommended Dosages

The recommended starting dose and the highest recommended dose of ALVESCO Inhalation Aerosol are listed in the following table.

Previous Therapy | Recommended Starting Dose | Highest Recommended Dose
Patients ≥ 12 years who received bronchodilators alone | 80 mcg twice daily | 160 mcg twice daily
Patients ≥ 12 years who received inhaled corticosteroids | 80 mcg twice daily | 320 mcg twice daily
Patients ≥ 12 years who received oral corticosteroids^1 | 320 mcg twice daily | 320 mcg twice daily
^1Prednisone should be reduced gradually, no faster than 2.5 mg/day on a weekly basis, beginning after at least 1 week of therapy with ALVESCO. Patients should be carefully monitored for signs of asthma instability, including monitoring of serial objective measures of airflow, and for signs of adrenal insufficiency during steroid taper and following discontinuation of oral corticosteroid therapy [see Warnings and Precautions (5.1)].

3 DOSAGE FORMS AND STRENGTHS

ALVESCO Inhalation Aerosol is available in the following two strengths: 80 mcg/actuation, and 160 mcg/actuation. The 80 mcg/actuation strength contains 60 actuations fill/canister, and the 160 mcg/actuation strength contains 60 actuations fill/canister.

ALVESCO 80 mcg Inhalation Aerosol is supplied with a brown plastic actuator with a red dust cap.

ALVESCO 160 mcg Inhalation Aerosol is supplied with a red plastic actuator with a red dust cap.

4 CONTRAINDICATIONS

4.1 Status Asthmaticus

ALVESCO is contraindicated in the primary treatment of status asthmaticus or other acute episodes of asthma where intensive measures are required.

4.2 Hypersensitivity

ALVESCO is contraindicated in patients with known hypersensitivity to ciclesonide or any of the ingredients of ALVESCO. Rare cases of hypersensitivity reactions with manifestations such as angioedema, with swelling of the lips, tongue and pharynx, have been reported.

5 WARNINGS AND PRECAUTIONS

5.1 Local Effects

In clinical trials, the development of localized infections of the mouth and pharynx with Candida albicans occurred in 32 of 3038 patients treated with ALVESCO. Of the 32 reported cases, 20 occurred in 1394 patients treated with a total daily dose of 320 mcg of ALVESCO or higher. Most cases of candida infection were mild to moderate. When such an infection develops, it should be treated with appropriate local or systemic (i.e. oral antifungal) therapy while remaining on treatment with ALVESCO, but at times therapy with ALVESCO may need to be interrupted. Patients should rinse the mouth after inhalation of ALVESCO.

5.2 Acute Asthma Episodes

ALVESCO is not a bronchodilator and is not indicated for rapid relief of bronchospasm or other acute episodes of asthma. Patients should be instructed to contact their physician immediately if episodes of asthma not responsive to their usual doses of bronchodilators occur during the course of treatment with ALVESCO. During such episodes, patients may require therapy with oral corticosteroids.

5.3 Immunosuppression

Persons who are using drugs that suppress the immune system are more susceptible to infections than healthy individuals. Chickenpox and measles, for example can have a more serious or even fatal course in susceptible children or adults using corticosteroids. In such children or adults who have not had these diseases or been properly immunized, particular care should be taken to avoid exposure. How the dose, route, and duration of corticosteroid administration affect the risk of developing a disseminated infection is not known. The contribution of the underlying disease and/or prior corticosteroid treatment to the risk is also not known. If exposed to chickenpox, prophylaxis with varicella zoster immune globulin (VZIG) may be indicated. If exposed to measles, prophylaxis with pooled intramuscular immunoglobulin (IG) may be indicated. (See the respective package inserts for complete VZIG and IG prescribing information.) If chickenpox develops, treatment with antiviral agents may be considered.

Inhaled corticosteroids should be used with caution, if at all, in patients with active or quiescent tuberculosis infection of the respiratory tract; untreated systemic fungal, bacterial, viral, or parasitic infections; or ocular herpes simplex.

5.4 Transferring Patients from Systemic Corticosteroid Therapy

Particular care is needed for patients who are transferred from systemically active corticosteroids to ALVESCO because deaths due to adrenal insufficiency have occurred in asthmatic patients during and after transfer from systemic corticosteroids to less systemically-available inhaled corticosteroids. After withdrawal from systemic corticosteroids, a number of months are required for recovery of hypothalamic-pituitary-adrenal (HPA) function.

Patients who have been previously maintained on 20 mg or more per day of prednisone (or its equivalent) may be most susceptible, particularly when their systemic corticosteroids have been almost completely withdrawn. During this period of HPA suppression, patients may exhibit signs and symptoms of adrenal insufficiency when exposed to trauma, surgery, or infection (particularly gastroenteritis) or other conditions associated with severe electrolyte loss. Although ALVESCO may provide control of asthma symptoms during these episodes, in recommended doses it supplies less than normal physiological amounts of corticosteroid systemically and does NOT provide the mineralocorticoid activity that is necessary for coping with these emergencies.

During periods of stress or a severe asthma attack, patients who have been withdrawn from systemic corticosteroids should be instructed to resume oral corticosteroids (in large doses) immediately and to contact their physicians for further instruction. These patients should also be instructed to carry a medical identification card indicating that they may need supplementary systemic corticosteroids during periods of stress or a severe asthma attack.

Patients requiring oral corticosteroids should be weaned slowly from systemic corticosteroid use after transferring to ALVESCO. Prednisone reduction can be accomplished by reducing the daily prednisone dose by 2.5 mg on a weekly basis during ALVESCO therapy [see Dosage and Administration (2)]. Lung function (FEV1 or AM PEFR), beta-agonist use, and asthma symptoms should be carefully monitored during withdrawal of oral corticosteroids. In addition to monitoring asthma signs and symptoms, patients should be observed for signs and symptoms of adrenal insufficiency, such as fatigue, lassitude, weakness, nausea and vomiting, and hypotension.

Transfer of patients from systemic steroid therapy to ALVESCO may unmask allergic conditions previously suppressed by the systemic steroid therapy, e.g., rhinitis, conjunctivitis, eczema, arthritis, and eosinophilic conditions.

During withdrawal from oral steroids, some patients may experience symptoms of systemically active steroid withdrawal, e.g., joint and/or muscular pain, lassitude, and depression, despite maintenance or even improvement of respiratory function.

5.5 Hypercorticism and Adrenal Suppression

ALVESCO will often help control asthma symptoms with less suppression of HPA function than therapeutically similar oral doses of prednisone. Since individual sensitivity to effects on cortisol production exists, physicians should consider this information when prescribing ALVESCO. Particular care should be taken in observing patients postoperatively or during periods of stress for evidence of inadequate adrenal response. It is possible that systemic corticosteroid effects such as hypercorticism and adrenal suppression may appear in a small number of patients particularly when ALVESCO is administered at higher than recommended doses over prolonged periods of time. If such effects occur, the dosage of ALVESCO should be reduced slowly, consistent with accepted procedures for reducing systemic corticosteroids and for management of asthma.

5.6 Reduction in Bone Mineral Density

Decreases in bone mineral density (BMD) have been observed with long-term administration of products containing inhaled corticosteroids. The clinical significance of small changes in BMD with regard to long-term outcomes is unknown. Patients with major risk factors for decreased bone mineral content, such as prolonged immobilization, family history of osteoporosis, or chronic use of drugs that can reduce bone mass (e.g. anticonvulsants and oral corticosteroids) should be monitored and treated with established standards of care.

5.7 Effect on Growth

Orally inhaled corticosteroids may cause a reduction in growth velocity when administered to pediatric patients. Monitor the growth of pediatric patients receiving ALVESCO routinely (e.g. via stadiometry). To minimize the systemic effects of orally inhaled corticosteroids, including ALVESCO, titrate each patient's dose to the lowest dosage that effectively controls his/her symptoms [see Use in Specific Populations (8.4)].

5.8 Glaucoma and Cataracts

Glaucoma, increased intraocular pressure, and cataracts have been reported following the administration of inhaled corticosteroids including ALVESCO. Therefore, close monitoring is warranted in patients with a change in vision or with a history of increased intraocular pressure, glaucoma, and/or cataracts.

In a comparator control study of one year treatment duration, 743 patients 18 years of age and older (mean age 43.1 years) with moderate persistent asthma were treated with ALVESCO 320 mcg twice daily and 742 were treated with a labeled dose of a comparator inhaled corticosteroid appropriate for the patient population. Patients had an ophthalmology examination that included visual acuity, intraocular pressure measurement, and a slit lamp examination at baseline, 4, 8 and 12 months. Lens opacities were graded using the Lens Opacification System III. After 52 weeks, CLASS I effects (minimally detected changes) were recorded in 36.1% of the ALVESCO-treated patients and in 38.4% of patients treated with the comparator inhaled corticosteroid. The more severe CLASS III effects were recorded in 8.1% of the ALVESCO-treated patients and 9.2% of patients treated with the comparator inhaled corticosteroid. Of those patients having a CLASS III effect, the incidence of posterior sub-capsular opacities was 0.9% and 0.5% in the ALVESCO- and comparator-treated patients respectively.

5.9 Bronchospasm

As with other inhaled asthma medications, bronchospasm, with an immediate increase in wheezing, may occur after dosing. If bronchospasm occurs following dosing with ALVESCO, it should be treated immediately with a fast-acting inhaled bronchodilator. Treatment with ALVESCO should be discontinued and alternative treatment should be instituted.

6 ADVERSE REACTIONS

Systemic and local corticosteroid use may result in the following:

- Candida albicans infection [see Warnings and Precautions (5.1)]
- Immunosupression [see Warnings and Precautions (5.3)]
- Hypercorticism and adrenal suppression [see Warnings and Precautions (5.5)]
- Growth effects [see Warnings and Precautions (5.7)]
- Glaucoma and cataracts [see Warnings and Precautions (5.8)]

6.1 Clinical Trial Experience

The safety data described below for adults and adolescents 12 years of age and older reflect exposure to ALVESCO in doses ranging from 80 mcg to 640 mcg twice daily in five double-blind placebo-controlled clinical trials. Studies with once daily dosing are omitted from the safety database because the doses studied once daily are lower than the highest recommended twice daily doses. The five studies were of 12 to 16 weeks treatment duration, one of which included a safety extension follow up of one year. In the 12 to 16 week treatment studies, 720 patients (298 males and 422 females) aged 12 years and older were exposed to ALVESCO. In the long-term safety trial, 197 patients (82 males and 115 females) with severe persistent asthma from one of the 12-week trials were re-randomized and treated for up to one year with ALVESCO 320 mcg twice daily. Safety information for pediatric patients 4 to 11 years of age, is obtained from once daily dosing studies. Two of these studies were designed with a 12-week double-blind treatment period followed by a long-term open label safety extension of one year, and one study was an open label safety study of one year duration [see Pediatric Use (8.4)].

Because clinical trials are conducted under widely varying conditions, adverse reaction rates observed in the clinical trials of a drug cannot be directly compared to rates in the clinical trials of another drug and may not reflect the rates observed in practice.

Adult and Adolescent 12 Years of Age and Older

Four of the five trials included a total of 624 patients ages 12 years and older (359 females and 265 males) with asthma of varying severity who were treated with ALVESCO 80 mcg, 160 mcg, or 320 mcg twice daily for 12 to 16 weeks. These studies included patients previously using either controller therapy (predominantly inhaled corticosteroids) or reliever therapy (bronchodilator therapy alone). In these trials, the mean age was 39.1 years, and the majority of the patients (79.0%) were Caucasian. In these trials, 52.3%, 59.8% and 54.1% of the patients in the ALVESCO 80 mcg, 160 mcg, and 320 mcg treatment groups, respectively, had at least one adverse event compared to 58.0% in the placebo group.

Table 1 includes adverse reactions for the recommended doses of ALVESCO that occurred at an incidence of ≥ 3% in any of the ALVESCO groups and which were more frequent with ALVESCO compared to placebo.

Table 1: Adverse Reactions with ≥ 3% Incidence Reported in Patients ≥ 12 Years of Age with ALVESCO in US Placebo-Controlled Clinical Trials in Patients Previously on Bronchodilators and/or Inhaled Corticosteroids
Adverse Reaction |  | ALVESCO
 | Placebo (N=507) % | 80 mcg BID (N=325) % | 160 mcg BID (N=127) % | 320 mcg BID (N=172) %
Headache | 7.3 | 4.9 | 11.0 | 8.7
Nasopharyngitis | 7.5 | 10.5 | 8.7 | 7.0
Sinusitis | 3.0 | 3.1 | 5.5 | 5.2
Pharyngolaryngeal pain | 4.3 | 4.3 | 2.4 | 4.7
Upper respiratory Inf. | 6.5 | 7.1 | 8.7 | 4.1
Arthralgia | 1.0 | 0.9 | 2.4 | 3.5
Nasal congestion | 1.6 | 1.8 | 5.5 | 2.9
Pain in extremity | 1.0 | 0.3 | 3.1 | 2.3
Back pain | 2.0 | 0.6 | 3.1 | 1.2

The following adverse reactions occurred in these clinical trials using ALVESCO with an incidence of less than 1% and occurred at a greater incidence with ALVESCO than with placebo.

Infections and Infestations: Oral candidiasis

Respiratory Disorders: Cough

Gastrointestinal Disorders: Dry mouth, nausea

General disorders and administrative site conditions: Chest discomfort

Respiratory, Thoracic, and Mediastinal Disorders: Dysphonia, dry throat

The fifth study was a 12-week clinical trial in asthma patients 12 years of age and older who previously required oral corticosteroids (average daily dose of oral prednisone of 12 mg/day), in which the effects of ALVESCO 320 mcg twice daily (n = 47) and 640 mcg twice daily (n = 49) were compared with placebo (n = 45) for the frequency of reported adverse reactions. The following adverse reactions occurred at an incidence of ≥ 3% in the ALVESCO-treated patients and were more frequent compared to placebo: sinusitis, hoarseness, oral candidiasis, influenza, pneumonia, nasopharyngitis, arthralgia, back pain, musculoskeletal chest pain, headache, urticaria, dizziness, gastroenteritis, face edema, fatigue, and conjunctivitis.

Pediatric Patients 4 to 11 Years of Age

The safety of ALVESCO in pediatric patients 4 to 11 years of age was evaluated in two studies in which ALVESCO 40 mcg, 80 mcg, and 160 mcg was administered once daily for 12 weeks [see Pediatric Use (8.4)].

Pediatric Patients under 4 Years of Age

Studies have not been conducted in patients under 4 years of age.

Long-Term Clinical Trials Experience

A total of 197 patients 12 years of age and older (82 males and 115 females) from one of the 12-week treatment placebo-controlled studies were re-randomized to ciclesonide 320 mcg twice daily and followed for one year. The safety profile from the one-year follow up was similar to that seen in the 12- and 16-week treatment studies. Long term safety information for pediatric patients 4 to 11 years of age is obtained from three open label one year safety studies [see Pediatric Use (8.4)].

6.2 Post-marketing Experience

In addition to adverse reactions identified from clinical trials, the following adverse reactions have been identified during worldwide post-marketing use of ciclesonide oral inhalation. Because these reactions are reported voluntarily from a population of uncertain size, it is not always possible to reliably estimate their frequency or establish a causal relationship to drug exposure.

Immune System Disorders: Immediate or delayed hypersensitivity reactions such as angioedema with swelling of the lips, tongue and pharynx.

7 DRUG INTERACTIONS

In clinical studies, concurrent administration of ciclesonide and other drugs commonly used in the treatment of asthma (albuterol, formoterol) had no effect on pharmacokinetics of des-ciclesonide [see Clinical Pharmacology (12.3)].

In vitro studies and clinical pharmacology studies suggested that des-ciclesonide has no potential for metabolic drug interactions or protein binding-based drug interactions [see Clinical Pharmacology (12.3)].

In a drug interaction study, co-administration of orally inhaled ciclesonide and oral ketoconazole, a potent inhibitor of cytochrome P450 3A4, increased the exposure (AUC) of des-ciclesonide by approximately 3.6-fold at steady state, while levels of ciclesonide remained unchanged.

8 USE IN SPECIFIC POPULATIONS

8.1 Pregnancy

Teratogenic Effects: Pregnancy Category C

Oral administration of ciclesonide in rats up to 900 mcg/kg/day (approximately 10 times the maximum human daily inhalation dose based on mcg/m^2/day) produced no teratogenicity or other fetal effects. However, subcutaneous administration of ciclesonide in rabbits at 5 mcg/kg/day (less than the maximum human daily inhalation dose based on mcg/m^2/day) or greater produced fetal toxicity. This included fetal loss, reduced fetal weight, cleft palate, skeletal abnormalities including incomplete ossifications, and skin effects. No toxicity was observed at 1 mcg/kg (less than the maximum human daily inhalation dose based on mcg/m^2).

There are no adequate and well-controlled studies in pregnant women. ALVESCO should be used during pregnancy only if the potential benefit justifies the potential risk to the fetus. Experience with oral corticosteroids since their introduction in pharmacologic as opposed to physiologic doses suggests that rodents are more prone to teratogenic effects from corticosteroids than humans. In addition, because there is a natural increase in corticosteroid production during pregnancy, most women will require a lower exogenous corticosteroid dose and many will not need corticosteroid treatment during pregnancy.

NONTERATOGENIC EFFECTS

Non-teratogenic Effects: Hypoadrenalism may occur in infants born of mothers receiving corticosteroids during pregnancy. Such infants should be carefully monitored.

8.3 Nursing Mothers

It is not known if ciclesonide is secreted in human milk. However, other corticosteroids are excreted in human milk. In a study with lactating rats, minimal, but detectable levels of ciclesonide were recovered in milk. Caution should be used when ALVESCO is administered to nursing women.

8.4 Pediatric Use

The safety and effectiveness of ALVESCO in children under 12 years of age have not been established.

Two randomized double-blind placebo-controlled studies were conducted to evaluate the efficacy of ALVESCO 40, 80, or 160 mcg administered once daily for 12 weeks in patients 4 to 11 years of age with asthma. These studies included 1018 patients previously using either controller therapy (predominately inhaled corticosteroids) or reliever therapy (bronchodilator therapy alone). The patients had a mean baseline percent predicated FEV1 of 68%. The primary efficacy endpoint was morning pre-dose FEV1. Other measures of efficacy included AM PEF, asthma symptoms, and rescue albuterol use. The studies showed inconsistent results and do not establish the efficacy of ALVESCO in patients 4 to 11 years of age.

The safety of ALVESCO was evaluated in 957 children between the ages of 4 and 11 who were treated with ALVESCO in the two controlled clinical studies, 2 open label one-year safety extensions of the controlled clinical studies, and one open label safety study. In the controlled studies, the distribution of adverse events in the ALVESCO and placebo groups was similar. The type of adverse events reported were similar to events reported in this patient population with other inhaled corticosteroids. The open label safety studies compared the safety of ALVESCO in doses up to 160 mcg once daily with an orally inhaled corticosteroid comparator. The types of adverse events seen were similar to those seen in the 12-week controlled studies.

Controlled clinical studies have shown that orally inhaled corticosteroids may cause a reduction in growth velocity in pediatric patients. In these studies, the mean reduction in growth velocity was approximately one centimeter per year (range 0.3 to 1.8 cm per year) and appears to be related to dose and duration of exposure. This effect has been observed in the absence of laboratory evidence of hypothalamic-pituitary-adrenal (HPA) axis suppression, suggesting that growth velocity is a more sensitive indicator of systemic corticosteroid exposure in pediatric patients than some commonly used tests of HPA axis function. The long-term effects of this reduction in growth velocity associated with orally inhaled corticosteroids, including the impact on final adult height are unknown. The potential for "catch up" growth following discontinuation of treatment with orally inhaled corticosteroids has not been adequately studied. The growth of pediatric patients receiving orally inhaled corticosteroids including ALVESCO should be monitored routinely (e.g., via stadiometry).

A 52-week, multi-center, double-blind, randomized, placebo-controlled parallel-group study was conducted to assess the effect of orally inhaled ciclesonide on growth rate in 609 pediatric patients with mild persistent asthma, aged 5 to 8.5 years. Treatment groups included orally inhaled ciclesonide 40 mcg or 160 mcg or placebo given once daily. Growth was measured by stadiometer height during the baseline, treatment and follow-up periods. The primary comparison was the difference in growth rates between ciclesonide 40 and 160 mcg and placebo groups. Conclusions cannot be drawn from this study because compliance could not be assured. There was no difference in efficacy measures between the placebo and the ALVESCO groups. Ciclesonide blood levels were also not measured during the one-year treatment period.

The potential growth effects of prolonged treatment with orally inhaled corticosteroids should be weighed against clinical benefits obtained and the availability of safe and effective noncorticosteroid treatment alternatives. To minimize the systemic effects of orally inhaled corticosteroids, including ALVESCO, each patient should be titrated to his/her lowest effective dose.

8.5 Geriatric Use

Clinical studies of ALVESCO did not include sufficient numbers of patients aged 65 years and older to determine whether they respond differently than younger patients. Other reported clinical experience has not identified differences in responses between the elderly and younger patients. In general, dose selection for an elderly patient should be cautious, usually starting at the low end of the dosing range reflecting the greater frequency of decreased hepatic, renal, or cardiac function and of concomitant disease or other drug therapy.

10 OVERDOSAGE

Chronic overdosage may result in signs/symptoms of hypercorticism [see Warnings and Precautions (5.5)]. ALVESCO was well tolerated following inhalation by healthy subjects of single doses of 2880 mcg. A single oral dose of up to 10 mg of ciclesonide in healthy subjects was well tolerated and serum cortisol levels were virtually unchanged in comparison with placebo treatment. Adverse reactions were of mild or moderate severity.

The median lethal doses in mice and rats after single oral and intraperitoneal administration were >2000 mg/kg and >200 mg/kg, respectively. These doses are >12000 and >2500 times the maximum recommended daily inhalation dose in adults on a mg/m^2 basis.

11 DESCRIPTION

The active component of ALVESCO 80 mcg Inhalation Aerosol, and ALVESCO 160 mcg Inhalation Aerosol is ciclesonide, a non-halogenated glucocorticoid having the chemical name pregna-1,4-diene-3,20-dione, 16,17-[[(R)-cyclohexylmethylene]bis(oxy)]-11-hydroxy-21-(2-methyl-1-oxopropoxy)-,(11β,16α). The empirical formula is C32H44O7 and its molecular weight is 540.7. Its structural formula is as follows:

Ciclesonide is a white to yellow-white powder. It is soluble in dehydrated alcohol, acetone, dichloromethane, and chloroform.

ALVESCO 80 mcg Inhalation Aerosol and ALVESCO 160 mcg Inhalation Aerosol are pressurized, metered-dose aerosol units fitted with a dose indicator. ALVESCO is intended for oral inhalation only. Each unit contains a solution of ciclesonide in propellant HFA-134a (1,1,1,2 tetrafluoroethane) and ethanol. After priming, ALVESCO 80 mcg delivers 100 mcg from the valve and 80 mcg of ciclesonide from the actuator. ALVESCO 160 mcg delivers 200 mcg from the valve and 160 mcg of ciclesonide from the actuator. This product delivers 50 microliters (59.3 milligrams) of solution as a fine particle mist from the valve with each actuation. The actual amount of drug delivered to the lung may depend on patient factors, such as the coordination between the actuation of the device and inspiration through the delivery system. ALVESCO should be “primed” by actuating 3 times prior to using the first dose from a new canister or when the inhaler has not been used for more than 10 days. Avoid spraying in the eyes or face while priming ALVESCO.

12 CLINICAL PHARMACOLOGY

12.1 Mechanism of Action

Ciclesonide, is a prodrug, that is enzymatically hydrolyzed to a pharmacologically active metabolite, C21-desisobutyryl-ciclesonide (des-ciclesonide or RM1) following oral inhalation. Des-ciclesonide has anti-inflammatory activity with affinity for glucocorticoid receptors that is 120 times greater than the parent compound and 12 times greater than dexamethasone. The clinical significance of these findings is unknown.

The precise mechanisms of corticosteroid action in asthma are unknown. Inflammation is recognized as an important component in the pathogenesis of asthma. Corticosteroids have been shown to have a wide range of inhibitory activities against multiple cell types (e.g., mast cells, eosinophils, basophils, lymphocytes, macrophages, and neutrophils) and mediators (e.g., histamine, eicosanoids, leukotrienes, and cytokines) involved in the asthmatic response. These anti-inflammatory actions of corticosteroids may contribute to their efficacy in asthma. Though effective for the treatment of asthma, corticosteroids do not affect asthma symptoms immediately. Individual patients will experience a variable time to onset and degree of symptom relief. Maximum benefit may not be achieved for four weeks or longer after starting treatment. When corticosteroids are discontinued, asthma stability may persist for several days or longer.

12.2 Pharmacodynamics

The effect of ciclesonide by oral inhalation on the HPA axis was assessed in adults with mild asthma in a 29-day placebo controlled study. Twenty-four-hour urinary free cortisol was assessed in a total of 59 adults who were randomized to 320 mcg or 640 mcg ALVESCO, a comparator corticosteroid, or placebo twice daily. At the end of 29 days of treatment, the mean (SE) change from baseline in 24 hr urinary free cortisol was -8.69 (5.6) mcg/day, -4.01 (5.03) mcg/day, and -8.84 (5.02) mcg/day for the placebo, ALVESCO 640 mcg/day, and ALVESCO 1280 mcg/day, respectively. The difference from placebo for the change from baseline in 24 hr urinary cortisol was +4.7 mcg/day [95% CI: -10.58; 19.93] and -0.16 mcg/day [95% CI: -15.20; 14.89] for the 640 mcg/day or 1280 mcg/day treatments, respectively. The effects observed with the comparator corticosteroid validate the sensitivity of the study to assess the effect of ciclesonide on the HPA axis.

12.3 Pharmacokinetics

Absorption

Ciclesonide and des-ciclesonide have negligible oral bioavailability (both are less than 1%) due to low gastrointestinal absorption and high first-pass metabolism. Serum concentrations of ciclesonide and des-ciclesonide were measured and compared following oral inhalation of 1280 mcg ALVESCO and intravenous administration of 800 mcg ciclesonide. The absolute bioavailability of ciclesonide was 22% and the relative systemic exposure of des-ciclesonide was 63%. The mean Cmax for des-ciclesonide was 1.02 ng/mL (range 0.6-1.5 ng/mL) in asthmatic patients following a single dose of 1280 mcg by oral inhalation. The mean Cmax (0.369 ng/mL) and AUC0-∞ (2.18 ng*hr/mL) of des-ciclesonide following multiple dose administration of ciclesonide 320 mcg once daily increased up to 26% compared to single dose administration.

Distribution

Following intravenous administration of 800 mcg of ciclesonide, the volumes of distribution of ciclesonide and des-ciclesonide was approximately 2.9 L/kg and 12.1 L/kg, respectively. The percentage of ciclesonide and des-ciclesonide bound to human plasma proteins averaged ≥ 99% each, with ≤ 1% of unbound drug detected in the systemic circulation. Des-ciclesonide is not significantly bound to human transcortin.

Metabolism

Ciclesonide is hydrolyzed to a biologically active metabolite, des-ciclesonide, by esterases. Des-ciclesonide undergoes further metabolism in the liver to additional metabolites mainly by the cytochrome P450 (CYP) 3A4 isozyme and to a lesser extent by CYP 2D6. The full range of potentially active metabolites of ciclesonide has not been characterized. After intravenous administration of ^14C-ciclesonide, 19.3% of the resulting radioactivity in the plasma is accounted for by ciclesonide or des-ciclesonide; the remainder may be a result of other, as yet, unidentified multiple metabolites.

Elimination

Following intravenous administration of 800 mcg of ciclesonide, the clearances of ciclesonide and des-ciclesonide were high (approximately 152 L/hr and 228 L/hr, respectively). ^14C-labeled ciclesonide was predominantly excreted via the feces after intravenous administration (66%) indicating that excretion through bile is the major route of elimination. Approximately 20% or less of des-ciclesonide was excreted in the urine. The mean half life of ciclesonide and des-ciclesonide was 0.71 hours and 6 to 7 hours respectively. Tmax of des-ciclesonide occurs at 1.04 hours following inhalation of ciclesonide.

Special Populations

Population pharmacokinetic analysis showed that characteristics of des-ciclesonide after oral inhalation of ciclesonide were not appreciably influenced by a variety of subject characteristics such as body weight, age, race, and gender.

Renal Insufficiency

Studies in renally-impaired patients were not conducted since renal excretion of des-ciclesonide is a minor route of elimination (≤ 20%).

Hepatic Insufficiency

Compared to healthy subjects, the systemic exposure of des-ciclesonide (Cmax and AUC) in patients with moderate to severe liver impairment increased in the range of 1.4 to 2.7 fold after 1280 mcg ex-actuator ciclesonide by oral inhalation. Dose adjustment in patients with liver impairment is not necessary.

Pediatric

In 2 clinical safety and efficacy studies conducted in patients 4 to 11 years of age with asthma, population pharmacokinetic samples were obtained in 53 patients for pharmacokinetic analysis. In these pediatric patients, treated with daily doses of 40, 80 or 160 mcg of ALVESCO, the median (min, max) Cmax values of des-ciclesonide were 41 pg/mL (not detectable, 146 pg/mL) (n=11), 113 pg/mL (35, 237 pg/mL) (n=13) and 128 pg/mL (12, 357 pg/mL) (n=14), respectively.

Drug-drug Interactions

In a drug interaction study, co-administration of orally inhaled ciclesonide and oral ketoconazole, a potent inhibitor of cytochrome P450 3A4, increased the exposure (AUC) of ciclesonide active metabolite, des-ciclesonide, by approximately 3.6-fold at steady state, while levels of ciclesonide remained unchanged [see Drug Interactions (7)].

In another single-dose drug interaction study, co-administration of orally inhaled ciclesonide and oral erythromycin, an inhibitor of cytochrome P450 3A4, had no effect on the pharmacokinetics of either ciclesonide and the active metabolite, des-ciclesonide, or erythromycin.

Based on in vitro studies in human liver microsomes, des-ciclesonide had no significant potential to inhibit or induce the metabolism of other drugs metabolized by CYP450 enzymes. The inhibitory potential of ciclesonide on CYP450 isoenzymes has not been studied. Based on in vitro human hepatocyte studies, ciclesonide and des-ciclesonide had no potential to induce major CYP450 isozymes.

In vitro studies demonstrated that the plasma protein binding of des-ciclesonide was not affected by warfarin or salicylic acid, indicating no potential for protein binding-based drug interactions.

In a population pharmacokinetic analysis including 98 subjects, co-administration of ALVESCO and albuterol had no effect on the pharmacokinetics of des-ciclesonide.

Concomitant administration of ALVESCO (640 mcg) and formoterol (24 mcg) did not change the pharmacokinetics of either des-ciclesonide or formoterol.

13 NONCLINICAL TOXICOLOGY

13.1 Carcinogenesis, Mutagenesis, Impairment of Fertility

Ciclesonide demonstrated no carcinogenic potential in a study of oral doses up to 900 mcg/kg/day (approximately 6 times the maximum human daily inhalation dose based on mcg/m^2/day) in mice for 104 weeks and in a study of inhalation doses up to 193 mcg/kg/day (approximately 2 times the maximum human daily inhalation dose based on mcg/m^2/day) in rats for 104 weeks.

Ciclesonide was not mutagenic in an Ames test or in a forward mutation assay and was not clastogenic in a human lymphocyte assay or in an in vitro micronucleus test. However, ciclesonide was clastogenic in the in vivo mouse micronucleus test. The concurrent reference corticosteroid (dexamethasone) in this study showed similar findings.

No evidence of impairment of fertility was observed in a reproductive study conducted in male and female rats both dosed orally up to 900 mcg/kg/day (approximately 10 times the maximum human daily inhalation dose based on mcg/m^2/day).

14 CLINICAL STUDIES

14.1 Asthma

Adults and Adolescents 12 years of Age and Older

The efficacy of ALVESCO was evaluated in six randomized double-blind, placebo-controlled, parallel-group clinical trials in adult and adolescent patients 12 years of age and older with mild persistent to severe persistent asthma. The six trials include two trials in which patients were treated with ALVESCO administered once daily for 12 weeks, two trials in which patients were treated with ALVESCO twice daily for 12 weeks, and two trials in which patients were treated with ALVESCO using once daily and twice daily dosing regimens for 12 or 16 weeks. These trials included a total of 2843 patients (1167 males and 1676 females) of whom 296 were adolescents 12-17 years of age. The primary efficacy endpoint in four of the six trials was the mean change from baseline in pre-dose FEV1 at endpoint (last observation). FEV1 was measured prior to the morning dose of study medication (at the end of the 24-hour dosing interval for once daily administration, and at the end of the 12-hour dosing interval for twice daily administration). In one of the six trials, the primary endpoint was the change from baseline in the average of the pre-dose FEV1 at Weeks 12 and 16, and in another trial, reduction of oral corticosteroid use was the primary efficacy endpoint. Additional efficacy variables were asthma symptoms, use of albuterol for rescue, AM PEF, nighttime awakenings, and withdrawal due to asthma worsening.

The two once daily dosing trials were identically designed and were conducted to evaluate the efficacy of ALVESCO 80, 160, and 320 mcg given once daily in the morning for 12 weeks in patients with mild to moderate asthma maintained on inhaled bronchodilators and/or corticosteroids. The results of these trials, along with other trials that explored twice daily dosing, indicate that once daily dosing is not the optimum dosing regimen for ALVESCO.

Four trials were designed to evaluate the efficacy of ALVESCO administered twice daily in patients with asthma who were previously maintained on bronchodilators alone, patients who were previously maintained on inhaled corticosteroids, and patients who were previously maintained on oral corticosteroids.

Patients Previously Maintained on Bronchodilators Alone

The efficacy of ALVESCO was studied in a randomized, double-blind, placebo-controlled trial in 691 patients with mild-to-moderate persistent asthma (mean baseline percent predicted FEV1 of 72%) previously using reliever therapy (bronchodilator therapy alone). In this trial, patients were treated with ALVESCO 160 mcg once daily in the morning for 16 weeks, ALVESCO 80 mcg twice daily for 16 weeks, or ALVESCO 80 mcg twice daily for 4 weeks followed by ALVESCO 160 mcg once daily in the morning for 12 weeks or placebo for 16 weeks. Compared to placebo, all ALVESCO doses showed statistically significant improvement at week 16 in AM pre-dose FEV1. However, the increase in AM pre-dose FEV1 in the patients treated with ALVESCO 80 mcg twice daily was significantly greater than that observed in patients treated with ALVESCO 160 mcg administered once daily. Compared to placebo, increases in AM pre-dose FEV1 were 0.12 L or 5.0 % for ALVESCO 160 mcg once daily, 0.24 L or 10.4 % for ALVESCO 80 mcg twice daily, 0.13 L or 5.0 % for ALVESCO 80 mcg twice daily for 4 weeks followed by ALVESCO 160 mcg once daily. Other measures of asthma control AM PEF, and need for rescue albuterol also improved in all the ALVESCO treatment groups compared to placebo but the improvement was greatest with the ALVESCO 80 mcg twice daily treatment arm. Discontinuations from the study for lack of efficacy were lower in the ALVESCO treatment groups compared to placebo. Fewer patients receiving ALVESCO experienced asthma worsening than did patients receiving placebo. The AM pre-dose FEV1 results are shown in Figure 1 below.

Figure 1: A 16-Week Double-Blind Clinical Trial Evaluating ALVESCO Administered Once Daily, Twice Daily, or Twice Daily Initially for 4 Weeks Followed by Once Daily for 12 Weeks, in Adult and Adolescent Patients with Mild-to-Moderate Asthma Previously Maintained on Bronchodilators Alone:

Patients Previously Maintained on Inhaled Corticosteroids

The efficacy of ALVESCO in asthma patients previously maintained on inhaled corticosteroids was evaluated in two randomized double-blind placebo controlled trials of 12-weeks treatment duration. In one trial, asthmatic patients with mild to moderate persistent asthma (mean baseline percent predicted FEV1 of 79%), previously maintained on controller therapy (predominantly inhaled corticosteroids) were treated with ALVESCO 160 mcg once daily in the morning, ALVESCO 80 mcg twice daily or placebo.

The AM pre-dose FEV1 results are shown in Figure 2 below.

Figure 2: A 12-Week Double-Blind Clinical Trial Evaluating ALVESCO Administered Once and Twice Daily in Adult and Adolescent Patients with Mild-to-Moderate Asthma Previously Maintained on Inhaled Corticosteroids:

Statistically significantly more increases in AM pre-dose FEV1 compared to placebo were seen at 12 weeks for ALVESCO 160 mcg once daily (0.14 L or 5.7%) and ALVESCO 80 mcg twice daily (0.19 L or 7.5%). Asthma symptoms scores, AM PEF, and decreased need for rescue albuterol remained relatively stable in the ALVESCO treatment groups compared to slight worsening in the placebo. Compared to placebo, fewer patients receiving ALVESCO experienced worsening of asthma.

In the other trial, 257 patients with moderate to severe persistent asthma (mean baseline percent predicted FEV1 of 54%) were treated with ALVESCO 160 or 320 mcg twice daily for 12 weeks. The AM pre-dose FEV1 results are shown in Figure 3 below.

Figure 3: A 12-Week Double-Blind Clinical Trial Evaluating ALVESCO Administered Twice Daily in Adult and Adolescent Patients with Severe Asthma:

Compared to placebo, both ALVESCO doses showed statistically significantly more improvement in pre-dose FEV1 (0.11 L or 8.6% and 0.18 L or 11.8%). Other measures of asthma control, AM PEF, symptoms, and need for rescue albuterol also showed improvement compared to placebo. Compared to placebo, fewer patients treated with ALVESCO experienced worsening of asthma.

Patients treated with ALVESCO were also less likely to discontinue study participation due to asthma deterioration.

Patients Previously Maintained on Oral Corticosteroids

In a 12-week double-blind clinical trial, 140 patients with severe persistent asthma (mean FEV1 at baseline 53% predicted) who had failed prior efforts to eliminate oral prednisone use and had established their lowest effective prednisone dose were randomized to ALVESCO given by inhalation aerosol at doses of 320 or 640 mcg twice daily or placebo. The average prednisone dose at baseline was approximately 12 mg/day. Compared to patients on placebo whose prednisone requirements increased by 4%, those treated with ALVESCO 320 mcg and 640 mcg twice daily significantly reduced their prednisone requirements by 47% and 62% respectively. At the same time, patients on ALVESCO maintained asthma control as reflected by lung function, symptoms, and need for rescue albuterol. A significantly larger percentage of patients on ALVESCO were able to reduce oral prednisone use by 50% or more as compared to placebo (64% and 77% of the patients treated with 320 mcg and 640 mcg respectively twice daily as compared with 33% of patients on placebo). There was no statistically significant difference observed with ALVESCO 640 mcg twice daily compared to ALVESCO 320 mcg twice daily.

Pediatric Patients 4 To 11 Years of Age

Two identically designed randomized, double-blind, parallel, placebo-controlled clinical trials of 12 weeks treatment duration were conducted in 1018 patients aged 4 to 11 years with asthma but efficacy was not established [see Pediatric Use (8.4)].

Pediatric Patients under 4 Years of Age

Clinical trials have not been conducted in pediatric patients under 4 years of age [see Pediatric Use (8.4)].

16 HOW SUPPLIED/STORAGE AND HANDLING

ALVESCO is available in the following strengths and canister presentations.

Micrograms per Actuation | Number of Actuations per Canister | Canister Weight | Canister per Box | NDC Number
ALVESCO 80 mcg | 60 | 6.1g | 1 | 54868-5989-0
ALVESCO 160 mcg | 60 | 6.1g | 1 | 54868-5990-0

ALVESCO 80 mcg Inhalation Aerosol is supplied with a brown plastic actuator with a red dust cap. Each actuation of the inhaler delivers 80 mcg of ciclesonide from the actuator.

ALVESCO 160 mcg Inhalation Aerosol is supplied with a red plastic actuator with a red dust cap. Each actuation of the inhaler delivers 160 mcg of ciclesonide from the actuator.

ALVESCO canisters are for use with ALVESCO Inhalation Aerosol actuators only. The actuators are fitted with a dose indicator and should not be used with other inhalation aerosol medications. The correct amount of medication in each actuation cannot be assured from the canister labeled to contain 60 actuations when the dose indicator display window shows zero even though the canister is not completely empty. The canister should be discarded when the dose indicator display window shows zero.

Store at 25°C (77°F).

Excursions between 15° and 30°C (59° and 86°F) are permitted (see USP). For optimal results, the canister should be at room temperature when used. Keep out of reach of children.

CONTENTS UNDER PRESSURE

Do not puncture. Do not use or store near heat or open flame. Exposure to temperatures above 49°C (120°F) may cause bursting. Never throw canister into fire or incinerator.

17 PATIENT COUNSELING INFORMATION

See FDA-Approved Patient Labeling accompanying the product.

17.1 Oral Candidiasis

Patients should be advised that localized infections with Candida albicans occurred in the mouth and pharynx in some patients. If oropharyngeal candidiasis develops, it should be treated with appropriate local or systemic (i.e., oral) antifungal therapy while still continuing with ALVESCO therapy, but at times therapy with the ALVESCO inhaler may need to be temporarily interrupted under close medical supervision. Rinsing the mouth after inhalation is advised.

17.2 Status Asthmaticus and Acute Asthma Symptoms

Patients should be advised that ALVESCO is not a bronchodilator and is not intended for use as rescue medication for acute asthma exacerbations. Acute asthma symptoms should be treated with an inhaled, short-acting beta2-agonist such as albuterol. The patient should be instructed to contact their physician immediately if there is deterioration of their asthma.

17.3 Immunosuppression

Patients who are on immunosuppressant doses of corticosteroids should be warned to avoid exposure to chickenpox or measles and, if exposed, to consult their physician without delay. Patients should be informed of potential worsening of existing tuberculosis, fungal, bacterial, viral, or parasitic infections, or ocular herpes simplex.

17.4 Hypercorticism and Adrenal Suppression

Patients should be advised that ALVESCO may cause systemic corticosteroid effects of hypercorticism and adrenal suppression. Additionally, patients should be instructed that deaths due to adrenal insufficiency have occurred during and after transfer from systemic corticosteroids. Patients should taper slowly from systemic corticosteroids if transferring to ALVESCO.

17.5 Reduction in Bone Mineral Density

Patients who are at an increased risk for decreased BMD should be advised that the use of corticosteroids may pose an additional risk and should be monitored and where appropriate, be treated for this condition.

17.6 Reduced Growth Velocity

Patients should be informed that orally inhaled corticosteroids, including ALVESCO, may cause a reduction in growth velocity when administered to pediatric patients. Physicians should closely follow the growth of children and adolescents taking corticosteroids by any route.

17.7 Use Daily for Best Effect

Patients should be advised to use ALVESCO at regular intervals, since its effectiveness depends on regular use. Maximum benefit may not be achieved for four weeks or longer after starting treatment. The patient should not increase the prescribed dosage but should contact their physician if symptoms do not improve or if the condition worsens. Patients should be instructed not to stop ALVESCO use abruptly. Patients should contact their physician immediately if use of ALVESCO is discontinued.

17.8 How to Use ALVESCO

Patients should use ALVESCO only with the actuator supplied with the product. When the dose indicator display window shows a red zone, approximately 20 inhalations are left, and a refill is required. Discard the inhaler when the indicator shows zero.

Manufactured for:
Sepracor Inc.
Marlborough, MA 01752 USA
Made in the United Kingdom

ALVESCO is a registered trademark of Nycomed GmbH and is used with permission.
US Patent Nos. 5,482,934; 6,264,923
©2007 Nycomed

July 2008
901139R01

Relabeling of "Additional Barcode Label" by:
Physicians Total Care, Inc.
Tulsa, OK 74146

ALVESCO® (ciclesonide) Inhalation Aerosol 80 mcg
ALVESCO® (ciclesonide) Inhalation Aerosol 160 mcg
For Oral Inhalation Only

Patient Instructions for Use

Read this leaflet carefully before starting to take this medicine. This leaflet provides a summary of information about ALVESCO, and does not contain the complete information about this medication. If you have any questions about ALVESCO, ask your health care provider or pharmacist.

What is ALVESCO?

Your health care provider has prescribed ALVESCO for the long-term treatment of your asthma. The medicine is available in 2 different strengths, and your health care provider has chosen the one most suitable for you.

ALVESCO contains ciclesonide, a man-made corticosteroid. Corticosteroids are natural anti-inflammatory substances found in the body. ALVESCO is used as maintenance treatment that helps prevent and control asthma symptoms because ALVESCO reduces airway inflammation.

When inhaled regularly, as prescribed by your health care provider, ALVESCO will help to prevent and control symptoms of asthma.

ALVESCO is not a bronchodilator. You should not use ALVESCO when you are having sudden symptoms of shortness of breath. Use an inhaled short-acting bronchodilator such as albuterol to relieve sudden symptoms of shortness of breath.

What Should I Tell My Health Care Provider Before Taking ALVESCO?

Tell your health care provider:

- If you are pregnant or plan to become pregnant.
- If you are breast-feeding.
- About any past or present medical problems or allergies.
- About all medicines that you are taking or plan to take, including those you can get without a prescription.
- If you have or had TB.
- If you are exposed to anyone with chicken pox or measles, or about any other infections you had before or while using ALVESCO.

Important Points to Remember About Using ALVESCO

- ALVESCO IS NOT A BRONCHODILATOR AND IS NOT INTENDED TO PROVIDE RAPID RELIEF OF BREATHING DIFFICULTIES DURING AN ASTHMA ATTACK.
- ALVESCO must be taken at regular intervals as recommended by your health care provider, and not as an emergency measure. Your health care provider may prescribe another medication (such as a bronchodilator) for rapid relief if an asthma attack occurs. Please contact your health care provider if:
  - an asthma attack does not respond to the other medication.
  - you require more of the other medication than usual.
- It is important that you inhale each dose of ALVESCO as your health care provider has advised. DO NOT inhale more doses or use your ALVESCO more often than your health care provider advises.
- It may take four weeks or longer to feel the full benefit of this medicine. Contact your health care provider if your symptoms do not improve in that time frame or if your condition worsens at any point during treatment.
- It is important that you continue to use ALVESCO regularly. Do not stop treatment even if you are feeling better unless told to do so by your health care provider.
- If you miss one dose of your medicine wait and take your regularly scheduled next dose.
- If you also use another medicine by inhalation, you should consult your health care provider for instructions on when to use it in relation to using ALVESCO.
- Use your ALVESCO Inhalation Aerosol canister with ALVESCO Inhalation Aerosol actuator only.
- Do not use the ALVESCO actuator with any other inhalation medications.

How to Use ALVESCO

Follow the instructions below. If you have any questions, ask your health care provider or pharmacist.

Your ALVESCO inhaler is fitted with a dose indicator which shows you how much of your medicine is left during use. The dose indicator display will move every tenth time you take a puff. The dose indicator display window will turn red when there are only 20 puffs remaining. This means that you need to replace your inhaler soon. The canister should be discarded when the dose indicator display window shows zero.

While your inhaler is fitted with a dose indicator to help determine the approximate number of puffs remaining, you should keep track of the number of puffs used from each canister of ALVESCO (see Step 8 below).

On the first use of your ALVESCO inhaler, as with all aerosol medicine, you should “test spray” the inhaler. To do this, remove the plastic cap and check the dose indicator on top of the inhaler to ensure that the dose indicator display window pointer is before the “60” inhalation mark before the first use. The “test spray” should also be done if the inhaler has not been used for more than 10 days. Spray 3 times into the air, away from the face by pressing firmly onto the center (not “off center”) of the dose indicator button, indicated by the middle of the three concentric rings on the button (see Figure 1). Be sure the canister is firmly seated in the plastic mouthpiece adapter before each use and that you press the inhaler slowly and firmly until it moves no further in the adapter for each spray.

You do not need to shake your ALVESCO inhaler before use. Check the dose indicator before the first use after the “test spray.” Check that the dose indicator display window shows that there are 60 inhalations left in the inhaler. If this is not the case, please return it to the pharmacy.

Steps for Inhalation:

1. Remove the plastic cap.
2. Breathe out as fully as you comfortably can. Hold the inhaler as shown in Figure 2. Close your lips around the mouthpiece, keeping your tongue below it.
3. While breathing in deeply and slowly, press down on the center (not “off center”) of the dose indicator with your finger. Fully depress the canister until it stops moving in the adapter while delivering your dose. When you have finished breathing in, hold your breath for about 10 seconds, or for as long as is comfortable. Note: It is normal to hear a soft click from the indicator as it counts down during use.
4. Take your finger completely off the center of the dose indicator and remove the inhaler from your mouth. Breathe out gently.
5. After use, always replace the cap to keep the mouthpiece clean. Note: The mouthpiece of your inhaler should be cleaned weekly with a clean, dry tissue or cloth.
6. After you finish taking your dose, rinse your mouth with water and spit it out. Do not swallow.
7. DO NOT WASH OR PUT ANY PART OF YOUR INHALER IN WATER.
8. DISCARD THE ALVESCO INHALER WHEN THE DOSE INDICATOR DISPLAY WINDOW SHOWS ZERO. The correct amount of medicine in each inhalation cannot be assured after this point. Note: If the inhaler is dropped, do not rely on the dose indicator. It is recommended to keep track of the number of inhalations taken from your inhaler based on your records.

POSSIBLE SIDE EFFECTS WITH ALVESCO

Serious Side Effects may include:

- Adrenal insufficiency (your adrenal gland can not produce enough steroids since you were on oral steroid medicine). If you took steroids by mouth and are having them decreased (tapered) or you are being switched to ALVESCO, you should be followed closely by your doctor. Death can occur. Tell your doctor right away about any symptoms such as feeling tired or exhausted, weakness, nausea, vomiting or symptoms of low blood pressure (such as dizziness or faintness). If you are under stress, such as with surgery, after surgery or trauma, you may need steroids by mouth again.
- Decreased bone mass (bone mineral density). Patients who use inhaled steroid medicines for a long time may have an increased risk of decreased bone mass which can affect bone strength. Talk with your healthcare provider about any questions about bone health.
- Possible increased risk of infection due to a weakened immune system with using steroid medicines.
- Bronchospasm (spasm of the breathing tubes) can occur, with wheezing right after a dose of the medicine. Stop using ALVESCO and use an inhaled short-acting bronchodilator right away, such as albuterol. Tell your healthcare provider right away so that a new maintenance medicine can be prescribed for your or your child's asthma.

The most common side effects with ALVESCO include: headache, nasopharyngitis, sinusitis, pharyngolaryngeal pain, upper respiratory infection, arthralgia, nasal congestion, pain in extremity and back pain.

Tell your doctor about any side effects that bother you or do not go away. These are not all of the possible side effects with ALVESCO. For more information, ask your doctor or pharmacist.

How to Store ALVESCO

For best results, store and use ALVESCO at room temperature.

Keep out of reach of children.

CONTENTS UNDER PRESSURE. Do not puncture. Do not use or store near heat or open flame. Exposure to temperature above 120°F (49°C) may cause bursting. Never throw canister into fire or incinerator.

DO NOT USE after the expiration date, shown as “Exp” on the package label or box.

Further Information

REMEMBER: This medicine has been prescribed for you by your health care provider. DO NOT give this medicine to anyone else.

This leaflet does not contain the complete information about your medication. If you have any questions, or are not sure about something, then you should ask your health care provider or pharmacist.

Because you may want to refer to this leaflet again, you may want to keep it until you have finished your medicine.

Manufactured for:
Sepracor Inc.
Marlborough, MA 01752 USA
Made in the United Kingdom

ALVESCO is a registered trademark of Nycomed GmbH and is used with permission.

US Patent Nos. 5,482,934; 6,264,923

©2007 Nycomed

July 2008
901139R01

PACKAGE LABEL

PACKAGE LABEL - PRINCIPAL DISPLAY PANEL - carton - 80mcg 60-count

Alvesco®

ciclesonide

Inhalation Aerosol

FOR ORAL INHALATION WITH ALVESCO ACTUATOR ONLY

Net Contents 6.1 g

Rx ONLY

80 mcg per actuation

60 Metered Actuations

PACKAGE LABEL

PACKAGE LABEL - PRINCIPAL DISPLAY PANEL - carton - 160mcg 60-count

Alvesco®

ciclesonide

Inhalation Aerosol

FOR ORAL INHALATION WITH ALVESCO ACTUATOR ONLY

Net Contents 6.1 g

Rx ONLY

160 mcg per actuation

60 Metered Actuations